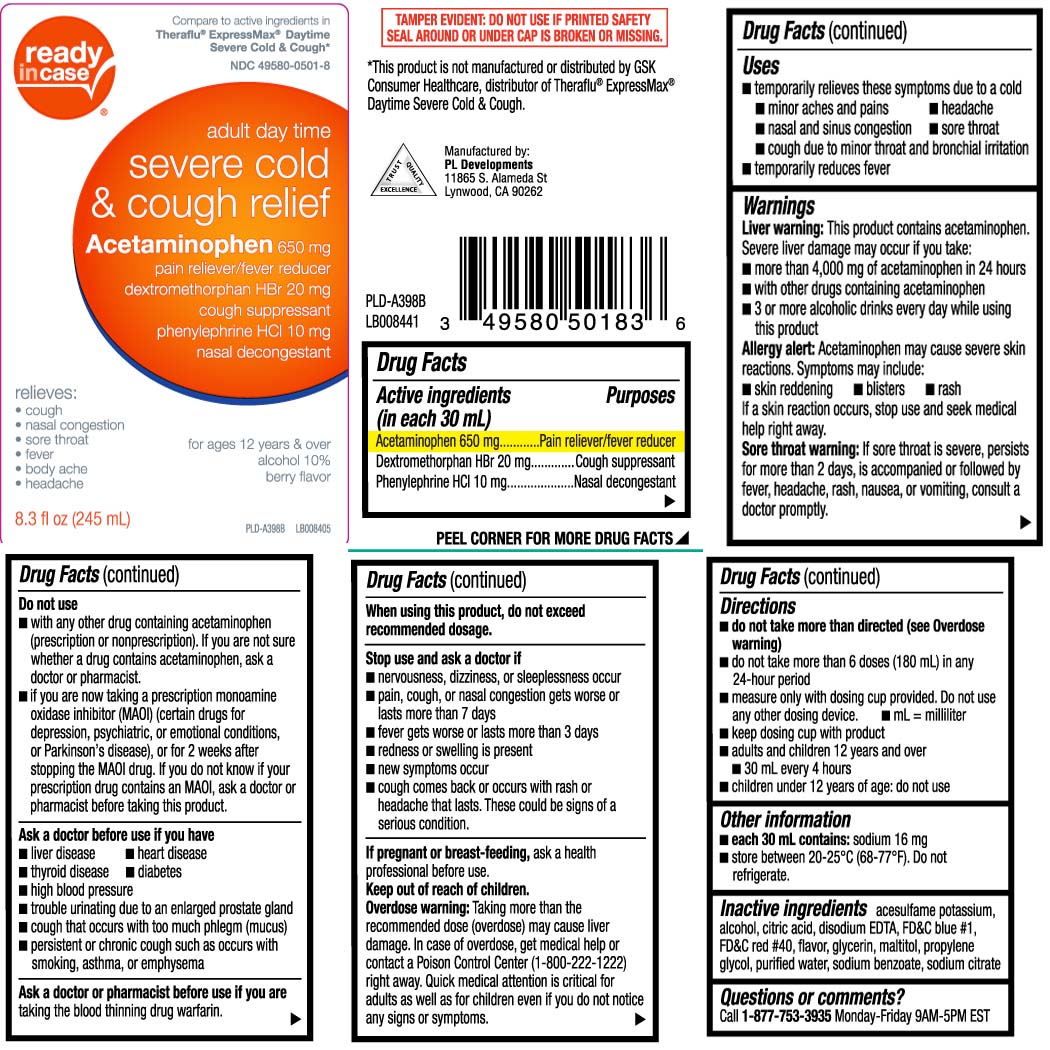 DRUG LABEL: Severe Cold and Cough Relief
NDC: 49580-0501 | Form: LIQUID
Manufacturer: P & L Development, LLC
Category: otc | Type: HUMAN OTC DRUG LABEL
Date: 20240415

ACTIVE INGREDIENTS: ACETAMINOPHEN 650 mg/30 mL; DEXTROMETHORPHAN HYDROBROMIDE 20 mg/30 mL; PHENYLEPHRINE HYDROCHLORIDE 10 mg/30 mL
INACTIVE INGREDIENTS: ACESULFAME POTASSIUM; ALCOHOL; ANHYDROUS CITRIC ACID; EDETATE DISODIUM; FD&C BLUE NO. 1; FD&C RED NO. 40; GLYCERIN; MALTITOL; PROPYLENE GLYCOL; WATER; SODIUM BENZOATE; TRISODIUM CITRATE DIHYDRATE

Drug Facts

Active ingredients (in each 30 mL)

Acetaminophen 650 mg

Dextromethorphan HBr 20 mg

Phenylephrine HCl 10 mg

Purposes

Pain reliever/fever reducer

Cough suppressant

Nasal decongestant

Uses

- temporarily relieves these symptoms due to a cold
  - minor aches and pains
  - headache
  - nasal and sinus congestion
  - sore throat
  - cough due to minor throat and bronchial irritation
- temporarily reduces fever

Warnings

Liver warning: This product contains acetaminophen. Severe liver damage may occur if you take:

- more than 4,000 mg of acetaminophen in 24 hours
- with other drugs containing acetaminophen
- 3 or more alcoholic drinks every day while using this product

Allergy alert: Acetaminophen may cause severe skin reactions. Symptoms may inclide:

- skin reddening
- blisters
- rash

If a skin reaction occurs, stop use and seek medical help right away.

Sore throat warning: If sore throat is severe, persists for more than 2 days, is accompanied or followed by fever, headache, rash, nausea, or vomiting, consult a doctor promptly.

Do not use

- if you are now taking a prescription monoamine oxidase inhibitor (MAOI) (certain drugs for depression, psychiatric or emotional conditions, or Parkinson's disease) or for 2 weeks after stopping the MAOI drug. If you do not know if your prescription drug contains an MAOI, ask a doctor or pharmacist before taking this product.
- with any other drug containing acetaminophen (prescription or non-prescription). If you are not sure whether a drug contains acetaminophen, ask a doctor or pharmacist.

Ask a doctor before use if you have

- liver disease
- heart disease
- diabetes
- high blood pressure
- thyroid disease
- trouble urinating due to an enlarged prostate gland
- cough that occurs with too much phlegm (mucus)
- persistent or chronic cough such as occurs with smoking, asthma, or emphysema

Ask a doctor or pharmacist before use if you are

taking the blood thinning drug warfarin.

When using this product,

do not exceed recommended dosage

Stop use and ask a doctor if

- nervousness, dizziness, or sleeplessness occur
- pain, cough, or nasal congestion gets worse or lasts more than 7 days
- fever gets worse or lasts more than 3 days
- redness or swelling is present
- new symptoms occur
- cough comes back or occurs with a rash or headache that lasts. These could be signs of a serious condition.

If pregnant or breast-feeding,

ask a health professional before use.

Keep out of reach of children.

Overdose warning: Taking more than the recommended dose (overdose) may cause liver damage. In case of overdose, get medical help or contact a Poison Control Center (1-800-222-1222) right away. Quick medical attention is critical for adults as well as for children even if you do not notice any signs or symptoms.

Directions

- do not take more than directed (see overdose warning)
- do not take more than 6 doses (180 mL) in any 24-hour period
- measure only with dosing cup provided. Do not use any other dosing device.
- mL= milliliter
- keep dosing cup with product
- adults and children 12 years and over
  - 30 mL every 4 hours
- chlldren under 12 years of age: do not use

Other information

- each 30 mL contains: sodium 16 mg
- store between 20-25ºC (68-77ºF). Do not refrigerate.

Inactive ingredients

acesulfame potassium, alcohol, citric acid, edetate disodium, FD&C blue #1, FD&C red #40, flavor, glycerin, maltitol, propylene glycol, purified water, sodium benzoate, sodium citrate

Questions or comments?

Call 1-877-753-3935 Monday-Friday 9AM-5PM EST

Principal Display Panel

Compare to active ingredients of Theraflu® ExpressMax® Daytime Severe Cold & Cough*

adult day time

severe cold & cough relief

Acetaminophen 650 mg

pain reliever/fever reducer

dextromethorphan HBr 20 mg

cough suppressant

Phenylephrine HCI 10 mg

nasal decongestion

relieves:

- cough
- nasal congestion
- sore throat
- fever
- body ache
- headache

for ages 12 years & over

alcohol 10%

Berry Flavor

fl oz (mL)

TAMPER EVIDENT: DO NOT USE IF PRINTED SAFETY SEAL AROUND OR UNDER CAP IS BROKEN OR MISSING.

*This product is not manufactured or distributed by GSK Consumer Healthcare, distributor of Theraflu® ExpressMax® Daytime Severe Cold & Cough.

Manufactured by:

PL Developments

11865 S. Alameda St

Lynwood, CA 90262

Product Label

READYinCASE Severe Cold & Cough Relief